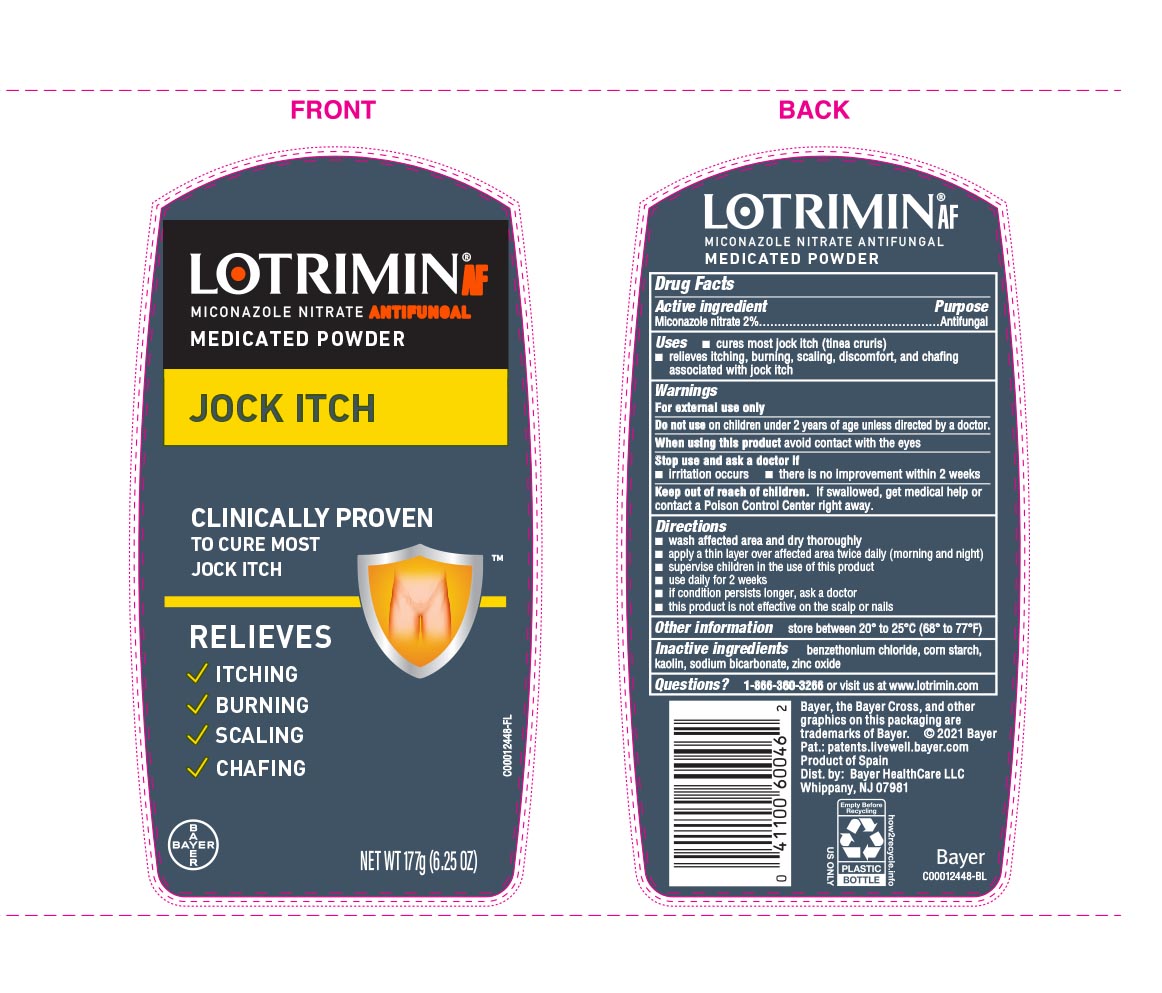 DRUG LABEL: Lotrimin
NDC: 11523-0150 | Form: POWDER
Manufacturer: Bayer HealthCare LLC.
Category: otc | Type: HUMAN OTC DRUG LABEL
Date: 20260116

ACTIVE INGREDIENTS: MICONAZOLE NITRATE 20 mg/1 g
INACTIVE INGREDIENTS: BENZETHONIUM CHLORIDE; STARCH, CORN; KAOLIN; SODIUM BICARBONATE; ZINC OXIDE

Lotrimin® AF Jock Itch Powder

Drug Facts

Active ingredient

Miconazole nitrate 2%

Purpose

Antifungal

Uses

- Cures most jock itch (tinea cruris)
- relieves Itching, burning, scaling, discomfort, and chafing associated with jock itch

Warnings

For external use only

Do not use on children under 2 years of age unless directed by a doctor.

When using this product

avoid contact with the eyes

Stop use and ask a doctor if

- irritation occurs
- if there is no improvement within 2 weeks

Keep out of reach of children. If swallowed, get medical help or contact a Poison Control Center right away.

Directions

- wash affected area and dry thoroughly
- sprinkle a thin layer over affected area twice daily (morning and night)
- supervise children in the use of this product
- use daily for 2 weeks
- if condition persists longer, ask a doctor
- this product is not effective on the scalp or nails

Other information

store between 20° to 25°C (68° to 77°F)

Inactive ingredients

benzethonium chloride, corn starch, kaolin, sodium bicarbonate, zinc oxide

PDP

LOTRIMIN ® AF

miconazole nitrate ANTIFUNGAL

MEDICATED POWDER
JOCK ITCH

CLINICALLY PROVEN

to cure most

jock itch

RELIEVES

- Itching
- Burning
- Scaling
- Chafing

NET WT 177g (6.25 OZ)